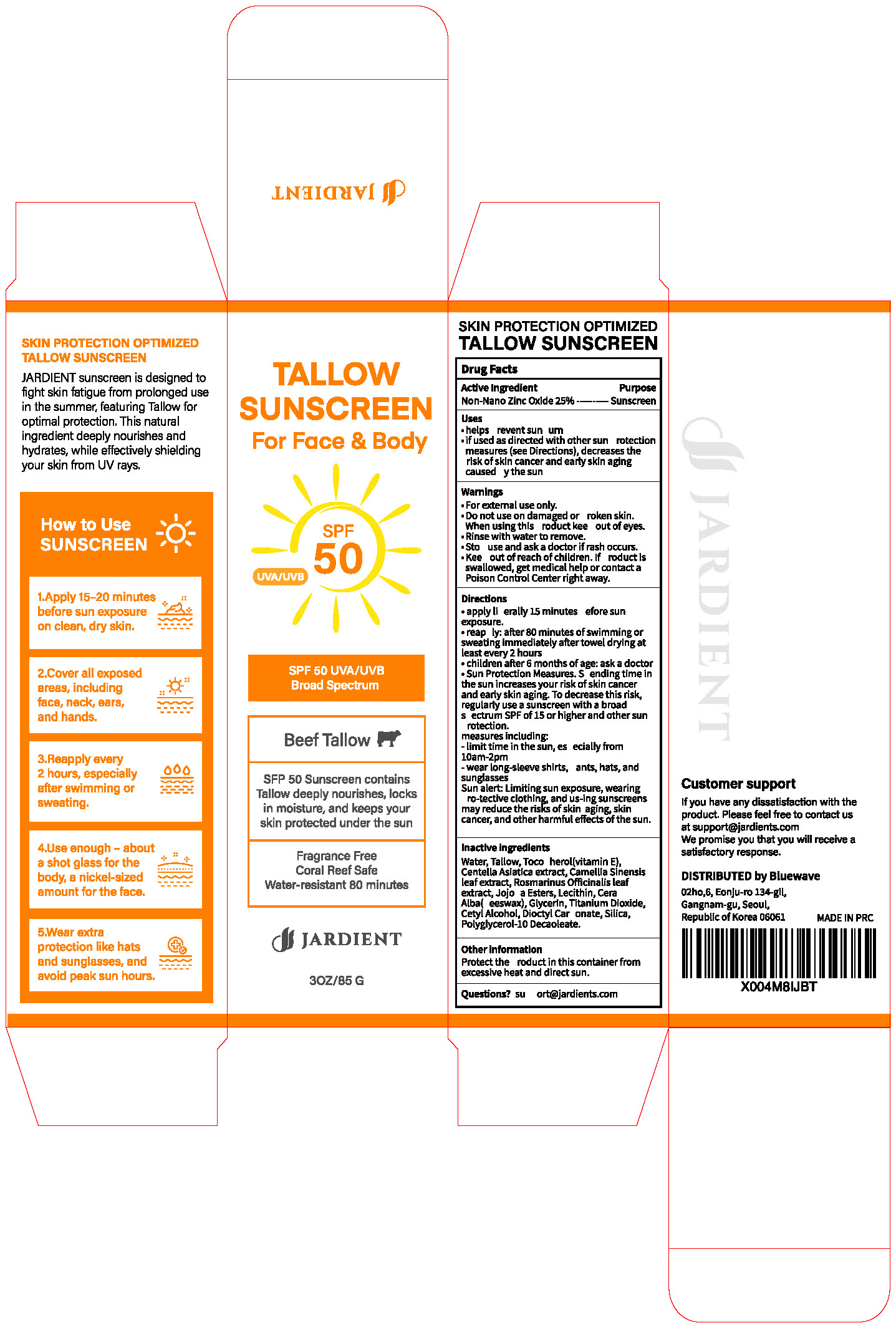 DRUG LABEL: Jardient TALLOW SUNSCREEN
NDC: 85646-005 | Form: CREAM
Manufacturer: GLOWVERA
Category: otc | Type: HUMAN OTC DRUG LABEL
Date: 20251107

ACTIVE INGREDIENTS: ZINC OXIDE 25 g/100 g
INACTIVE INGREDIENTS: SORBITAN OLEATE; POLYSORBATE 80; PROPYLENE GLYCOL; BUTYROSPERMUM PARKII (SHEA) OIL; POTASSIUM CETYL PHOSPHATE; WATER; ETHYLHEXYL METHOXYCINNAMATE; C13-14 ISOPARAFFIN; PHENOXYETHANOL; STEARETH-20; ETHYLHEXYLGLYCERIN; DIMETHICONE; EDETATE DISODIUM; XANTHAN GUM; ALUMINUM HYDROXIDE; LAURETH-7; GLYCERIN; CETEARYL ALCOHOL; POLYACRYLAMIDE (1500 MW); PANTHENOL; OCTISALATE; STEARETH-2; .ALPHA.-TOCOPHEROL ACETATE; PARAFFINUM LIQUIDUM; SODIUM ACRYLATE/SODIUM ACRYLOYLDIMETHYLTAURATE COPOLYMER (4000000 MW); SILICA; C12-15 ALKYL BENZOATE; ISOHEXADECANE; TOCOPHEROL; TITANIUM DIOXIDE

Active Ingredient

Non-Nano Zinc Oxide 25%

use

.helps prevent sunburn

.if used as directed with other sun protectionmeasures(see Directions),decreases therisk of skin cancer and early skin agingcaused by the sun

Warning

.For external use only

.Do not use on damaged or broken skin.When using this product keep out of eyes

.Rinse with water to remove.

.Stop use and ask a doctorif rash occurs.

.Keep out of reach of children.lf product isswallowed, get medical help or contact aPoison Control Center right away.

Directions

.apply liberally 15 minutes before sun exposure.

.reapply: after 80 minutes of swimming or sweating immediately after towel drying at least every 2 hours

children after 6 months of age: ask a doctor

Sun Protection Measures. Spending time in the sun increases your risk of skin cancer and early skin aging. To decrease this risk, regularly use a sunscreen with a broad spectrum SPF of 15 or higher and other sun protection.

measures including:

-limit time in the sun, especially from10am-2pm

-wear long-sleeve shirts, pants, hats, and sunglasses

Sun alert: Limiting sun exposure, wearing protective clothing, and using sunscreens may reduce the risks of skin aging, skin cancer, and other harmful effects of the sun.

Inactive ingredients

Water, Tallow, Tocopherol(vitamin E),Centella Asiatica extract, Camellia Sinensisleaf extract, Rosmarinus Officinalis leafextract,Jojoba Esters, Lecithin, CeraAlba(beeswax),Glycerin,Titanium Dioxide.Cetyl Alcohol, Dioctyl Carbonate, Silica,Polyglycerol-10 Decaoleate.

none

none

none

none

none

Questions?

support@jardients.com

Purpose

Sunscreen